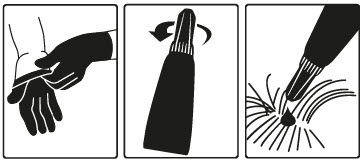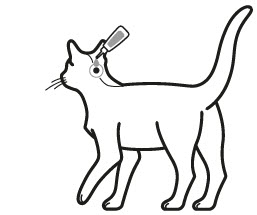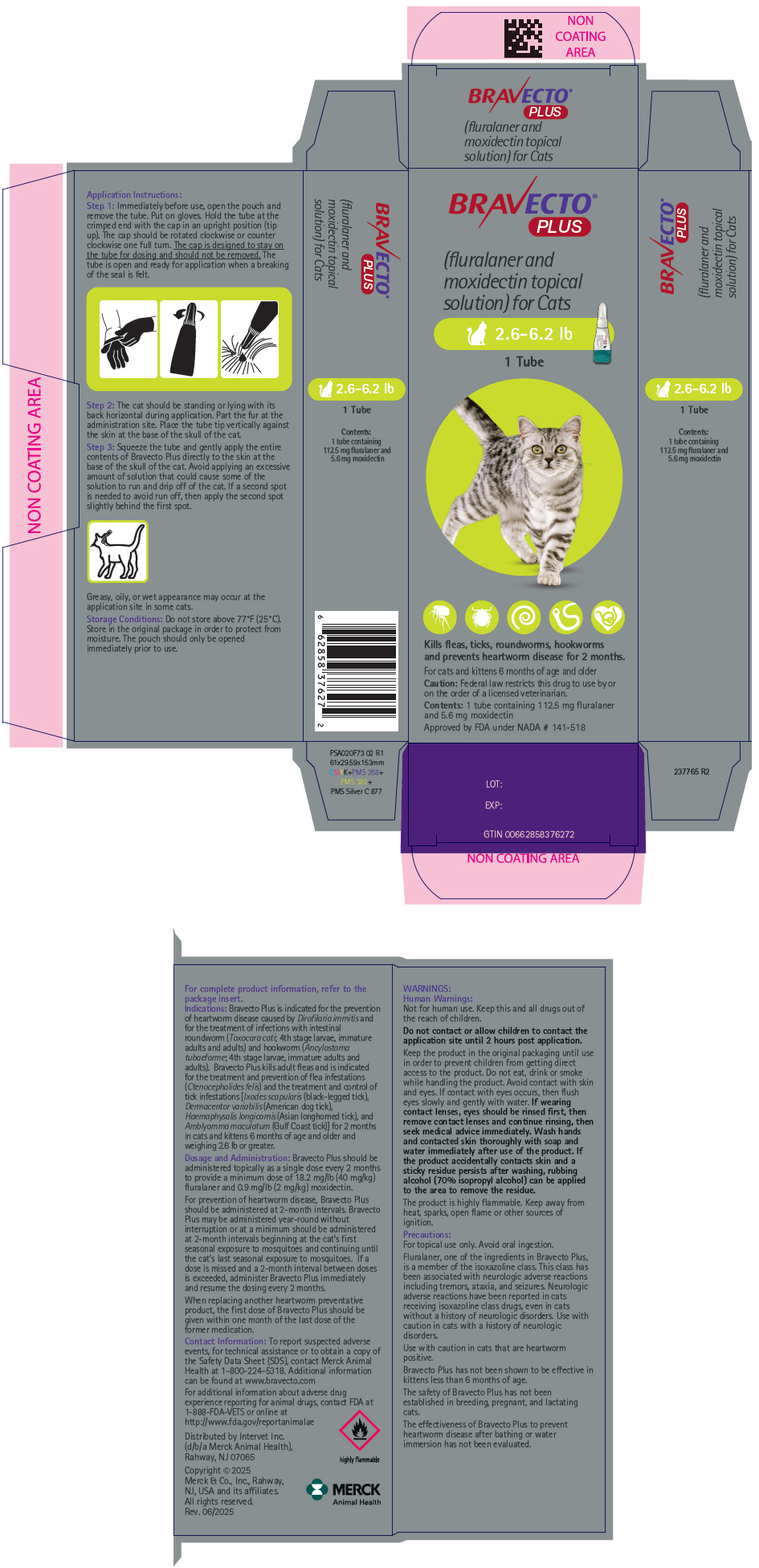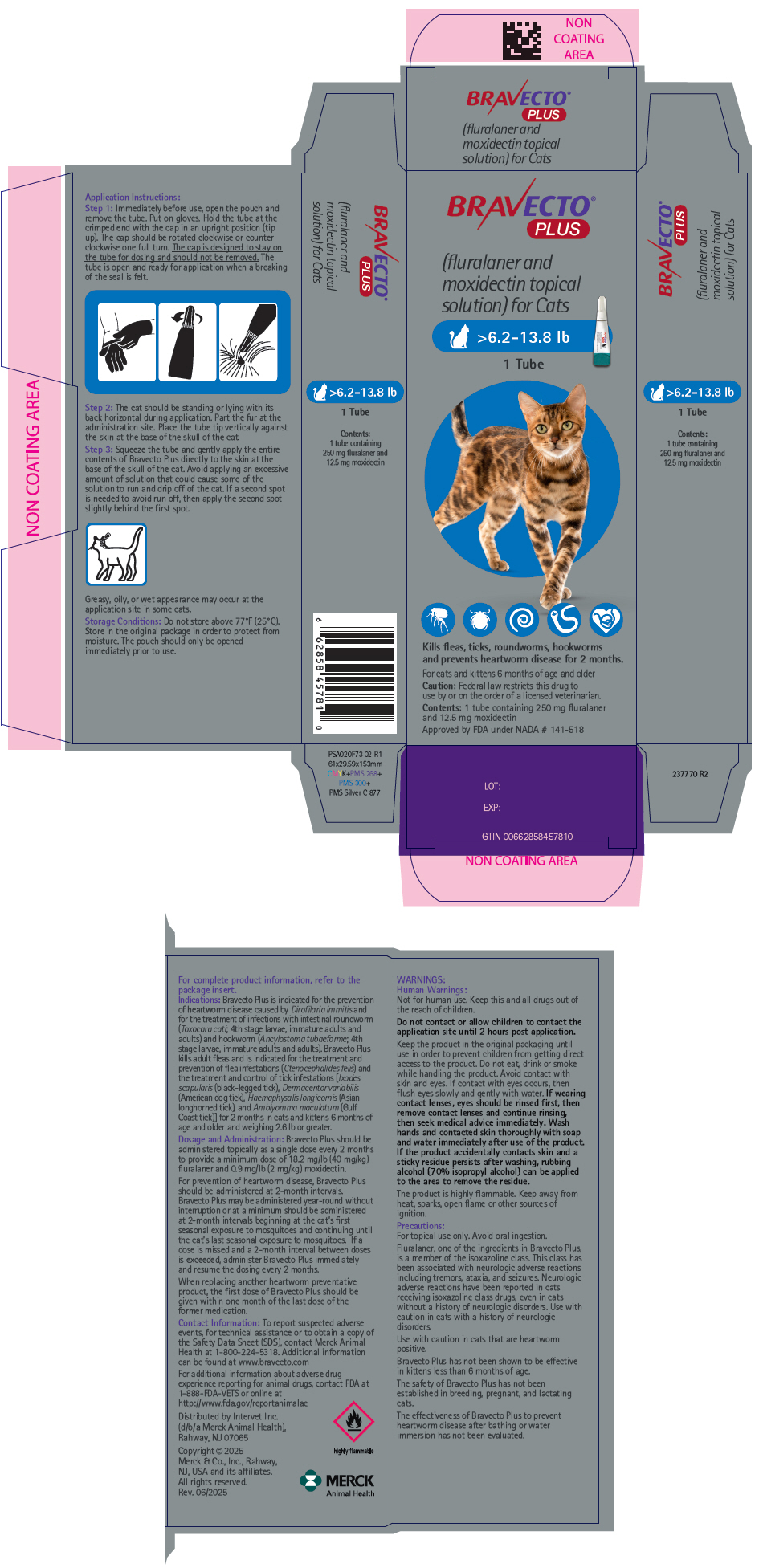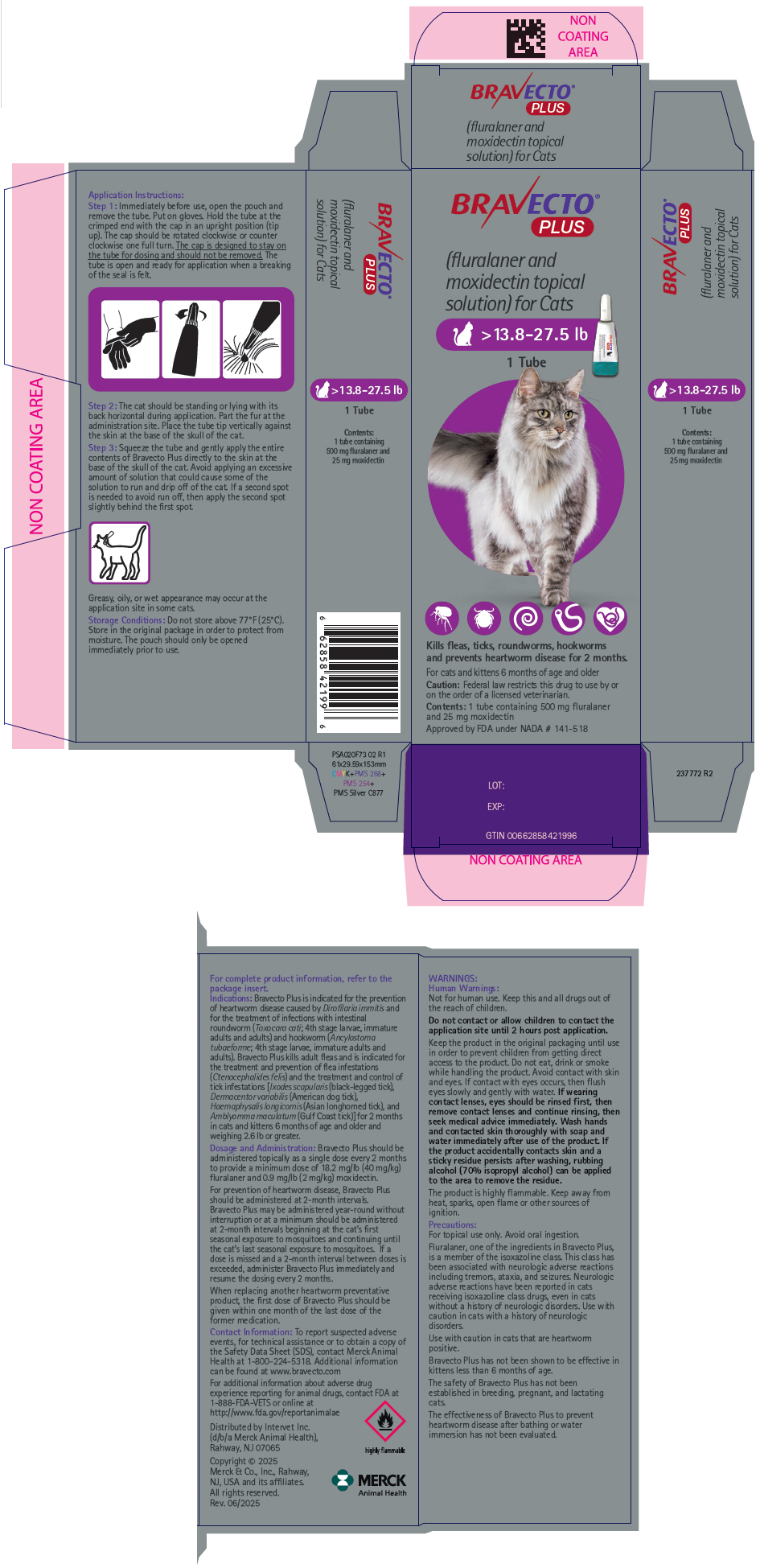 DRUG LABEL: Bravecto Plus
NDC: 0061-5996 | Form: SOLUTION
Manufacturer: Merck Sharp & Dohme Corp.
Category: animal | Type: PRESCRIPTION ANIMAL DRUG LABEL
Date: 20260120

ACTIVE INGREDIENTS: FLURALANER 112.5 mg/1 1; MOXIDECTIN 5.6 mg/1 1

BRAVECTO® PLUS
(fluralaner and moxidectin topical solution) for Cats

Caution:

Federal law restricts this drug to use by or on the order of a licensed veterinarian.

Description:

Each tube is formulated to provide a minimum dose of 18.2 mg/lb (40 mg/kg) fluralaner and 0.9 mg/lb (2 mg/kg) moxidectin. Each milliliter contains 280 mg of fluralaner and 14 mg of moxidectin.

The chemical name of fluralaner is (±)-4-[5-(3,5-dichlorophenyl)-5-(trifluoromethyl)- 4,5-dihydroisoxazol-3-yl]-2-methyl-N-[2-oxo-2-(2,2,2- trifluoroethylamino)ethyl]benzamide. The chemical name of moxidection is (2aE,4E,5'R,6R,6'S,8E,11R,13S,15S,17aR,20R,20aR,20bS)-6'-[(E)-1,3-Dimethyl-1-butenyl]-5',6,6',7,10,11,14,15,17a,20,20a,20b-dodecahydro-20,20b-dihydroxy-5',6,8,19-tetramethylspiro[11,15-methano-2H,13H,17H-furo[4,3,2-pq][2,6] benzodioxacyclooctadecin-13,2'-[2H]pyran]-4',17(3'H)-dione 4'-(E)-(O-methyloxime). Inactive ingredients: dimethylacetamide, glycofurol, diethyltoluamide, acetone, butylhydroxytoluene

Indications:

Bravecto Plus is indicated for the prevention of heartworm disease caused by Dirofilaria immitis and for the treatment of infections with intestinal roundworm (Toxocara cati; 4th stage larvae, immature adults and adults) and hookworm (Ancylostoma tubaeforme; 4th stage larvae, immature adults and adults). Bravecto Plus kills adult fleas and is indicated for the treatment and prevention of flea infestations (Ctenocephalides felis) and the treatment and control of tick infestations [Ixodes scapularis (black-legged tick), Dermacentor variabilis (American dog tick) and Haemaphysalis longicornis (Asian longhorned tick), and Amblyomma maculatum (Gulf Coast tick)] for 2 months in cats and kittens 6 months of age and older and weighing 2.6 lb or greater.

Dosage and Administration:

Bravecto Plus should be administered topically as a single dose every 2 months according to the Dosage Schedule below to provide a minimum dose of 18.2 mg/lb (40 mg/kg) fluralaner and 0.9 mg/lb (2 mg/kg) moxidectin.

For prevention of heartworm disease, Bravecto Plus should be administered at 2-month intervals. Bravecto Plus may be administered year-round without interruption or at a minimum should be administered at 2-month intervals beginning at the cat's first seasonal exposure to mosquitoes and continuing until the cat's last seasonal exposure to mosquitoes. If a dose is missed and a 2-month interval between doses is exceeded, administer Bravecto Plus immediately and resume the dosing every 2 months.

When replacing a monthly heartworm preventative product, the first dose of Bravecto Plus should be given within one month of the last dose of the former medication.

Dosing Schedule:
Body Weight Ranges (lb) | Fluralaner content (mg/tube) | Moxidectin content (mg/tube) | Tubes Administered
2.6 – 6.2 | 112.5 | 5.6 | One
>6.2 – 13.8 | 250 | 12.5 | One
>13.8 – 27.5 [Cats over 27.5 lb should be administered the appropriate combination of tubes.] | 500 | 25 | One

A veterinarian or veterinary technician should demonstrate or instruct the pet owner regarding the appropriate technique for applying Bravecto Plus topically to cats prior to first use.

Step 1: Immediately before use, open the pouch and remove the tube. Put on gloves. Hold the tube at the crimped end with the cap in an upright position (tip up). The cap should be rotated clockwise or counter clockwise one full turn. The cap is designed to stay on the tube for dosing and should not be removed. The tube is open and ready for application when a breaking of the seal is felt.

Step 2: The cat should be standing or lying with its back horizontal during application. Part the fur at the administration site. Place the tube tip vertically against the skin at the base of the skull of the cat.

Step 3: Squeeze the tube and gently apply the entire contents of Bravecto Plus directly to the skin at the base of the skull of the cat. Avoid applying an excessive amount of solution that could cause some of the solution to run and drip off of the cat. If a second spot is needed to avoid run off, then apply the second spot slightly behind the first spot.

Greasy, oily, or wet appearance may occur at the application site in some cats.

Contraindications:

There are no known contraindications for the use of the product.

WARNINGS:

Human Warnings:

Not for human use. Keep this and all drugs out of the reach of children.

Do not contact or allow children to contact the application site until 2 hours post application.

Keep the product in the original packaging until use in order to prevent children from getting direct access to the product. Do not eat, drink or smoke while handling the product. Avoid contact with skin and eyes. If contact with eyes occurs, then flush eyes slowly and gently with water. If wearing contact lenses, eyes should be rinsed first, then remove contact lenses and continue rinsing, then seek medical advice immediately. Wash hands and contacted skin thoroughly with soap and water immediately after use of the product. If the product accidentally contacts skin and a sticky residue persists after washing, rubbing alcohol (70% isopropyl alcohol) can be applied to the area to remove the residue.

The product is highly flammable. Keep away from heat, sparks, open flame or other sources of ignition.

Precautions:

For topical use only. Avoid oral ingestion (see Animal Safety).

Fluralaner, one of the ingredients in Bravecto Plus, is a member of the isoxazoline class. This class has been associated with neurologic adverse reactions including tremors, ataxia, and seizures. Neurologic adverse reactions have been reported in cats receiving isoxazoline class drugs, even in cats without a history of neurologic disorders. Use with caution in cats with a history of neurologic disorders.

Use with caution in cats that are heartworm positive (see Animal Safety).

Bravecto Plus has not been shown to be effective in kittens less than 6 months of age.

The safety of Bravecto Plus has not been established in breeding, pregnant, and lactating cats.

The effectiveness of Bravecto Plus to prevent heartworm disease after bathing or water immersion has not been evaluated.

Adverse Reactions:

In a well-controlled U.S. field study, which included a total of 176 treated cats (135 with Bravecto Plus and 41 with a monthly topical active control), there were no serious adverse reactions.

Percentage of Cats with Adverse Reactions (AR) in the Field Study
Adverse Reaction | Bravecto Plus Group: Percent of Cats with the AR During the 120-Day Study (n=135 cats) | Active Control Group: Percent of Cats with the AR During the 120-Day Study (n=41 cats)
Vomiting | 5.9% | 12.2%
Alopecia (not at application site) | 5.2% | 2.4%
Pruritus | 4.4% | 12.2%
Application site pruritus | 4.4% | 4.9%
Diarrhea | 3.7% | 7.3%
Lethargy | 3.7% | 9.8%
Dry Skin | 3.0% | 0.0%
Elevated alanine aminotransferase (ALT) [ALT was greater than twice the upper reference range of 100 IU/L. These cats also had mild elevations of aspartate aminotransferase (AST) (less than twice the upper reference range of 100 IU/L). No clinical signs associated with liver disease were noted in these cats.] | 3.0% | 0.0%
Hypersalivation | 1.5% | 1.5%
Application site alopecia | 0.7% | 0.0%

In well-controlled laboratory effectiveness studies, the following adverse reactions were seen after application of Bravecto Plus: pyrexia, tachypnea, mydriasis, pruritus, scabbing, and bloody stool.

Foreign Market Experience: The following adverse events were reported voluntarily during post-approval use of the product in cats in foreign markets: polydipsia, swelling of chin and lips, periorbital swelling, blepharospasm, pruritus, erythema, aggression, agitation, pyrexia, mydriasis, hypersalivation, hyperactivity, alopecia, and excessive grooming. These adverse events occurred within 48 hours of administration.

In a European field study for fluralaner topical solution for cats, there were three reports of facial dermatitis in humans after close contact with the application site which occurred within 4 days of application. In foreign market experience reports for Bravecto Plus, one veterinarian experienced tingling and numbness of the fingers, hand, and arm, and swelling of the hand and arm after getting Bravecto Plus on her fingers. Additional signs, including blurred vision and disorientation, occurred after taking an antihistamine.

Post-Approval Experience (2022):

The following adverse events are based on post-approval adverse drug experience reporting for Bravecto Plus. Not all adverse events are reported to FDA/CVM. It is not always possible to reliably estimate the adverse event frequency or establish a causal relationship to product exposure using these data.

The following adverse events reported in cats are listed in decreasing order of reporting frequency:

Application site alopecia, lethargy, hypersalivation, vomiting, anorexia, application site disorders (including pruritus, erythema, and lesions), behavioral disorders (including hiding and hyperactivity), ataxia, generalized pruritus, muscle tremor, alopecia, weight loss, and diarrhea.

Contact Information:

To report suspected adverse events, for technical assistance or to obtain a copy of the Safety Data Sheet (SDS), contact Merck Animal Health at 1-800-224-5318. Additional information can be found at www.bravecto.com

For additional information about adverse drug experience reporting for animal drugs, contact FDA at 1-888-FDA-VETS or online at http://www.fda.gov/reportanimalae

Clinical Pharmacology:

Peak fluralaner concentrations are achieved between 3 and 21 days following topical administration and the elimination half-life ranges between 11 and 18 days. Peak moxidectin concentrations are achieved between 1 and 5 days following topical administration and the elimination half-life ranges between 20 and 30 days.

Mode of Action:

Fluralaner is for systemic use and belongs to the class of isoxazoline-substituted benzamide derivatives. Fluralaner is an inhibitor of the arthropod nervous system. The mode of action of fluralaner is the antagonism of the ligand-gated chloride channels (gamma-aminobutyric acid (GABA)-receptor and glutamate-receptor).

Moxidectin is for systemic use and is a semisynthetic derivative of nemadectin, belonging to the milbemycin group of macrocyclic lactones. It binds to gamma-aminobutyric acid (GABA) and glutamate-gated chloride channels of the nerves and muscles of the parasite resulting in hyperpolarization, paralysis and death.

Effectiveness:

In two well-controlled laboratory studies, Bravecto Plus was 100% effective against induced heartworm infections when administered 2 months prior to infection. Bravecto Plus was not effective when administered more than 2 months prior to infection.

In well-controlled laboratory studies, Bravecto Plus was effective against naturally and experimentally induced adult and experimentally induced 4th stage larval and immature adult Toxocara cati and Ancylostoma tubaeforme infections in cats.

In a well-controlled laboratory study, Bravecto Plus killed 100% of fleas within 12 hours after treatment and reduced the numbers of live fleas on cats by >99% within 12 hours after treatment or infestation for 2 months. In well-controlled laboratory studies, Bravecto Plus demonstrated >90% effectiveness against Dermacentor variabilis 48 hours after treatment or infestation for 2 months but failed to demonstrate ≥ 90% effectiveness beyond 2 months. In well-controlled laboratory studies, Bravecto Plus demonstrated ≥ 98.1% effectiveness against Ixodes scapularis and Haemaphysalis longicornis 48 hours after treatment or infestation for 2 months. In well-controlled laboratory studies, Bravecto Plus demonstrated 100% effectiveness against Amblyomma maculatum 72 hours after treatment or infestation for 2 months but failed to demonstrate≥ 90% effectiveness beyond 2 months.

Animal Safety:

Margin of Safety Study: In a margin of safety study, Bravecto Plus was administered topically to 9- to 13-week-old (mean age 12 weeks) kittens at 1×, 3×, and 5× the maximum labeled dose of 93.0 mg fluralaner/kg and 4.7 mg moxidectin/kg at three, 8-week intervals (10 kittens per group). The kittens in the control group (0×) were treated with mineral oil. There were no clinically-relevant, treatment-related effects on physical examination, body weights, food consumption, clinical pathology (hematology, clinical chemistries, coagulation tests, serum amyloid A, and urinalysis), gross pathology, histopathology, or organ weights. Single incidences of self-limiting hypersalivation in three kittens (one kitten in the 1× group and two kittens in the 3× group) and pruritus at the administration site in one kitten in the 3× group were observed on the day of dose administration. Cosmetic changes at the application site included matting/clumping/spiking of hair, wetness, or a greasy appearance.

Oral Safety Studies: In an oral safety study, one dose of Bravecto Plus was administered orally to 4- to 9-month-old kittens at the maximum labeled dose of 93.0 mg fluralaner/kg and 4.7 mg moxidectin/kg. The kittens in the control group were administered saline orally. There were no clinically-relevant, treatment-related effects on physical examination, body weights, food consumption, or clinical pathology (hematology, clinical chemistries, coagulation tests, serum amyloid A, and urinalysis). Five of six treated kittens experienced hypersalivation. One treated kitten experienced vomiting 2 hours after administration and another 8 hours after treatment. Treated kittens had reduced food consumption on the day of treatment.

In an oral safety study for fluralaner topical solution for cats, four out of six cats experienced coughing immediately after oral administration of the maximum labeled dose of 93.0 mg fluralaner/kg.

In a pilot oral safety study, adult cats orally administered 0.5× or 1× the maximum labeled dose of Bravecto Plus had foaming hypersalivation for up to five minutes and reduced food consumption on the day of dosing. One cat exhibited transient lacrimation from one eye during the first 15 minutes after dosing.

Safety in cats infected with adult heartworm (Dirofilaria immitis): Bravecto Plus was administered topically to cats infected with adult heartworm at 1× or 3× the maximum labeled dose of 93.0 mg fluralaner/kg and 4.7 mg moxidectin/kg (8 cats per group). The cats in the control group (0×) received mineral oil topically. Two untreated cats were found dead prior to dosing. There were no clinically-relevant, treatment-related effects on body weights, clinical pathology (hematology, clinical chemistry, and coagulation profile), gross pathology or histopathology. Self-limiting hypersalivation due to grooming was observed on the day of treatment in both treatment groups (6/8 cats in the 1× group and 7/8 cats in the 3× group). In addition, three treated cats (2/8 cats in the 1× group and 1/8 cats in the 3× group) developed adverse neurologic signs during the study and were euthanized due to quality-of-life concerns. Clinical signs in one cat in the 1× group included vomiting, depression, vocalization, and ataxia 38 days after dosing. A second cat in the 1× group had neurologic signs that included ataxia, paresis, and muscle tremors 25 days after dosing. A cat in the 3× group exhibited depression, dehydration, a hunched position, and inability to stand 22 days after dosing. Heartworms were found in the epidural space in the second cat of the 1× group and the cat in the 3× group.

Field Safety Study: In a well-controlled field study, Bravecto Plus was used concurrently with other medications, such as vaccines, anthelmintics, antibiotics and steroids. No adverse reactions were observed from the concurrent use of Bravecto Plus with other medications.

Storage Conditions:

Do not store above 77°F (25°C). Store in the original package in order to protect from moisture. The pouch should only be opened immediately prior to use.

How Supplied:

Bravecto Plus is available in three tube sizes to treat cats ranging in weight from 2.6 lb – 27.5 lb (1.2 kg to 12.5 kg). Each tube is packaged individually in a pouch. Product may be supplied in 1 or 2 tubes per carton.

Approved by FDA under NADA # 141-518

Formulated in France
Distributed by: Intervet Inc. (d/b/a Merck Animal Health), Rahway,
NJ 07065
Copyright © 2025 Merck & Co., Inc., Rahway, NJ, USA and its
affiliates. All rights reserved.

Rev: 06/2025

237766 R2

MERCK
Animal Health

PRINCIPAL DISPLAY PANEL - 112.5 mg/5.6 mg Tube Pouch Carton

BRAVECTO®
PLUS

(fluralaner and
moxidectin topical
solution) for Cats

2.6-6.2 lb

1 Tube

Kills fleas, ticks, roundworms, hookworms
and prevents heartworm disease for 2 months.

For cats and kittens 6 months of age and older

Caution: Federal law restricts this drug to use by or
on the order of a licensed veterinarian.

Contents: 1 tube containing 112.5 mg fluralaner
and 5.6 mg moxidectin

Approved by FDA under NADA # 141-518

PRINCIPAL DISPLAY PANEL - 250 mg/12.5 mg Tube Pouch Carton

BRAVECTO®
PLUS

(fluralaner and
moxidectin topical
solution) for Cats

>6.2-13.8 lb

1 Tube

Kills fleas, ticks, roundworms, hookworms
and prevents heartworm disease for 2 months.

For cats and kittens 6 months of age and older

Caution: Federal law restricts this drug to
use by or on the order of a licensed veterinarian.

Contents: 1 tube containing 250 mg fluralaner
and 12.5 mg moxidectin

Approved by FDA under NADA # 141-518

PRINCIPAL DISPLAY PANEL - 500 mg/25 mg Tube Pouch Carton

BRAVECTO®
PLUS

(fluralaner and
moxidectin topical
solution) for Cats

>13.8-27.5 lb

1 Tube

Kills fleas, ticks, roundworms, hookworms
and prevents heartworm disease for 2 months.

For cats and kittens 6 months of age and older

Caution: Federal law restricts this drug to use by or
on the order of a licensed veterinarian.

Contents: 1 tube containing 500 mg fluralaner
and 25 mg moxidectin

Approved by FDA under NADA # 141-518